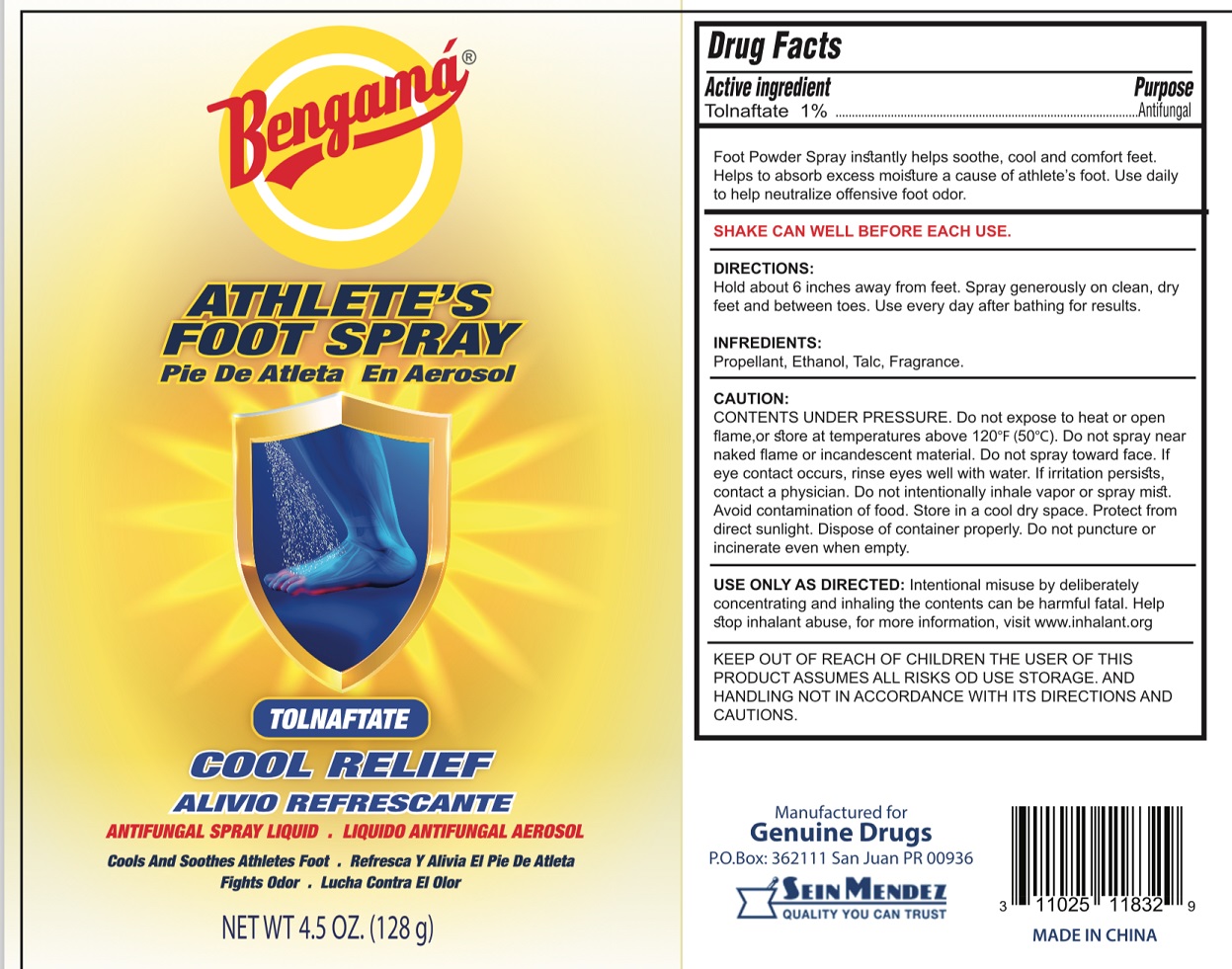 DRUG LABEL: Bengama -
NDC: 69666-833 | Form: AEROSOL, SPRAY
Manufacturer: Genuine Drugs
Category: otc | Type: HUMAN OTC DRUG LABEL
Date: 20181017

ACTIVE INGREDIENTS: TOLNAFTATE 10 mg/1 g
INACTIVE INGREDIENTS: PROPANE; ISOBUTANE; ALCOHOL; TALC

Bengama-TOLNAFTATE

Active ingredient

Tolnaftate 1 %

Purpose

Antifungal

INDICATIONS AND USAGE

Foot Powder Spray instantly helps soothe, cool and comfort feet. Helps to absorb excess moisture a cause of athlete's foot. Use daily to help neutralize offensive foot odor.

CAUTION:

CONTENTS UNDER PRESSURE. Do not expose to heat or open flame, or store at temperatures above 120°F (50°C). Do not spray near naked flame or incandescent material. Do not spray toward face. If eye contact occurs, rinse eyes well with water. If irritation persists, contact a physician. Do not intentionally inhale vapor or spray mist. Avoid contamination of food. Store in a cool dry space. Protect from direct sunlight. Dispose of container properly. Do not puncture or incinerate even when empty.

USE ONLY AS DIRECTED: Intentional misuse by deliberately concentrating and inhaling the contents can be harmful fatal. Help stop inhalant abuse. for more information, visit www.inhalant.org

KEEP OUT OF REACH OF CHILDREN THE USER OF THIS PRODUCT ASSUMES ALL RISKS OD USE STORAGE. AND HANDLING NOT IN ACCORDANCE WITH ITS DIRECTIONS AND CAUTIONS.

DIRECTIONS:

SHAKE CAN WELL BEFORE EACH USE.

Hold about 6 inches away from feet. Spray generously on clean, dry feet and between toes. Use every day after bathing for results.

INGREDIENTS:

Propellant, Ethanol, Talc, Fragrance.

ATHLETE'S FOOT SPRAY

COOL RELIEF

ANTIFUNGAL SPRAY LIQUID

Cools And Soothes Athletes Foot

Fights Odor

Manufactured for

Genuine Drugs

P.O.Box: 362111 San Juan PR 00936

SEIN MENDEZ

Quality you can trust

MADE IN CHINA